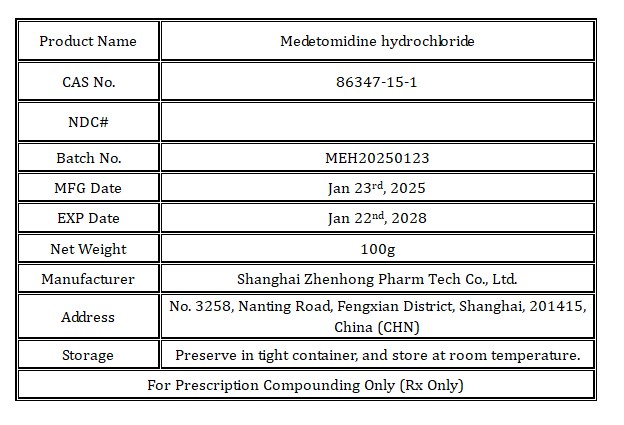 DRUG LABEL: Medetomidine HCl
NDC: 86228-153 | Form: POWDER
Manufacturer: Shanghai Zhenhong Pharm Tech Co., Ltd.
Category: other | Type: BULK INGREDIENT - ANIMAL DRUG
Date: 20250626

ACTIVE INGREDIENTS: Medetomidine hydrochloride 1 kg/1 kg

Medetomidine HCl